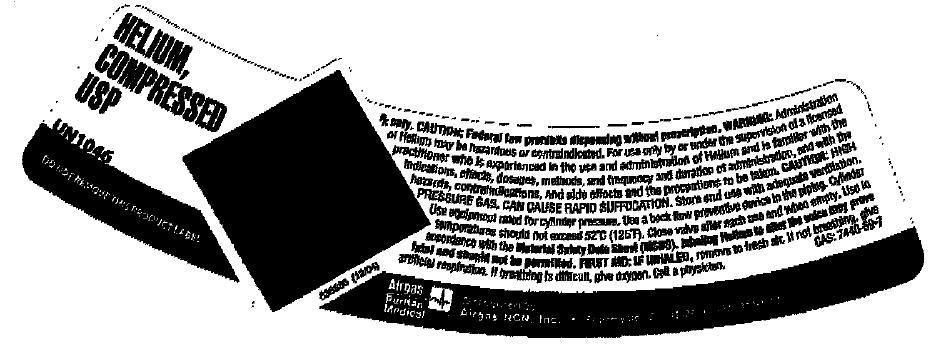 DRUG LABEL: Helium
NDC: 58789-005 | Form: GAS
Manufacturer: Airgas Northern California and Nevada, Inc.
Category: prescription | Type: HUMAN PRESCRIPTION DRUG LABEL
Date: 20100614

ACTIVE INGREDIENTS: Helium 999 mL/1 L

helium

PACKAGE LABEL

HELIUM, COMPRESSED USP
UN 1046
DO NOT REMOVE THIS PRODUCT LABEL
RX ONLY. CAUTION: Federal law prohibits dispensing without prescription. WARNING: Administration of Helium may be hazardous or contraindicated. For use only by or under supervision of a licensed practitioner who is experienced in the use and administration of Helium and is familiar with the indications, effects, dosage, methods, and frequency and duration of administration, and with the hazards, contraindications. And side effects and the precautions to be taken. CAUTION: HIGH PRESSURE GAS, CAN CAUSE RAPID SUFFOCATION. Store and use with adequate ventilation. Use equipment rated for cylinder pressure. Use a back flow preventative device in the piping. Cylinder temperatures should not exceed 52C (125F). Close valve after each use and when empty. Use in accordance with the Material Safety Data Sheets (MSDS) FIRST AID: IF INHALED, remove to fresh air. If not breathing, give artificial respiration. If breathing is difficult give oxygen. Call a physican. CAS 7440-59-Airgas